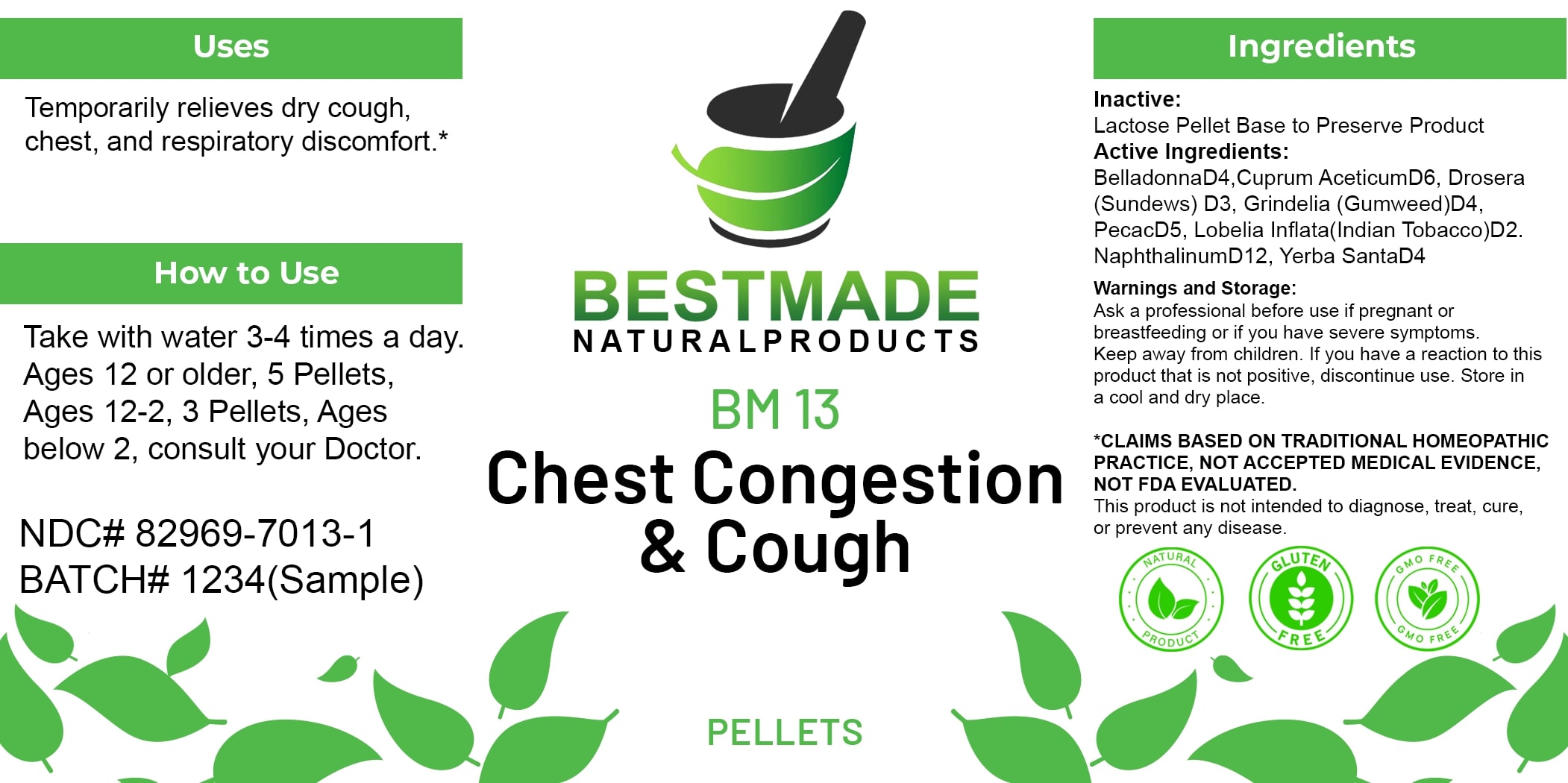 DRUG LABEL: Bestmade Natural Products BM13 Pellets
NDC: 82969-7013 | Form: TABLET, SOLUBLE
Manufacturer: Bestmade Natural Products
Category: homeopathic | Type: HUMAN OTC DRUG LABEL
Date: 20250408

ACTIVE INGREDIENTS: ATROPA BELLADONNA 30 [hp_C]/30 [hp_C]; CUPRIC ACETATE 30 [hp_C]/30 [hp_C]; IPECAC 30 [hp_C]/30 [hp_C]; DROSERA ROTUNDIFOLIA 30 [hp_C]/30 [hp_C]; LOBELIA INFLATA WHOLE 30 [hp_C]/30 [hp_C]; NAPHTHALENE 30 [hp_C]/30 [hp_C]; ERIODICTYON CALIFORNICUM LEAF 30 [hp_C]/30 [hp_C]; GRINDELIA HIRSUTULA FLOWERING TOP 30 [hp_C]/30 [hp_C]
INACTIVE INGREDIENTS: LACTOSE 30 [hp_C]/30 [hp_C]

BM13 Pellets

DOSAGE AND ADMINISTRATION

How to Use

Take with water 3-4 times a day. Ages 12 or older, 5 Pellets, Ages 12-2, 3 Pellets, Ages below 2, consult your Doctor.

Uses

Temporarily relieves dry cough, chest, and respiratory discomfort.*

*CLAIMS BASED ON TRADITIONAL HOMEOPATHIC PRACTICE. NOT ACCEPTED MEDICAL EVIDENCE. NOT FDA EVALUATED.

This product is not intended to diagnose, treat, cure, or prevent any disease.

INACTIVE INGREDIENT

Ingredients

Inactive: Lactose Pellet Base to Preserve Product

ACTIVE INGREDIENT

Active Ingredients: BelladonnaD4, Cuprum AceticumD6, Drosera (Sundews) D3, Grindelia (Gumweed)D4, IpecacD5, Lobelia Inflata(Indian Tobacco)D2, NaphthalinumD12, Yerba SantaD4

KEEP OUT OF REACH OF CHILDREN

Warnings and Storage:

Ask a professional before use if pregnant or breastfeeding or if you have severe symptoms. Keep away from children. If you have a reaction to this product that is not positive, discontinue use. Store in a cool and dry place.

Warnings and Storage:

Ask a professional before use if pregnant or breastfeeding or if you have severe symptoms. Keep away from children. If you have a reaction to this product that is not positive, discontinue use. Store in a cool and dry place.

*CLAIMS BASED ON TRADITIONAL HOMEOPATHIC PRACTICE. NOT ACCEPTED MEDICAL EVIDENCE. NOT FDA EVALUATED.

This product is not intended to diagnose, treat, cure, or prevent any disease.

Uses

Temporarily relieves dry cough, chest, and respiratory discomfort.*

*CLAIMS BASED ON TRADITIONAL HOMEOPATHIC PRACTICE. NOT ACCEPTED MEDICAL EVIDENCE. NOT FDA EVALUATED.

This product is not intended to diagnose, treat, cure, or prevent any disease.

Entire package label